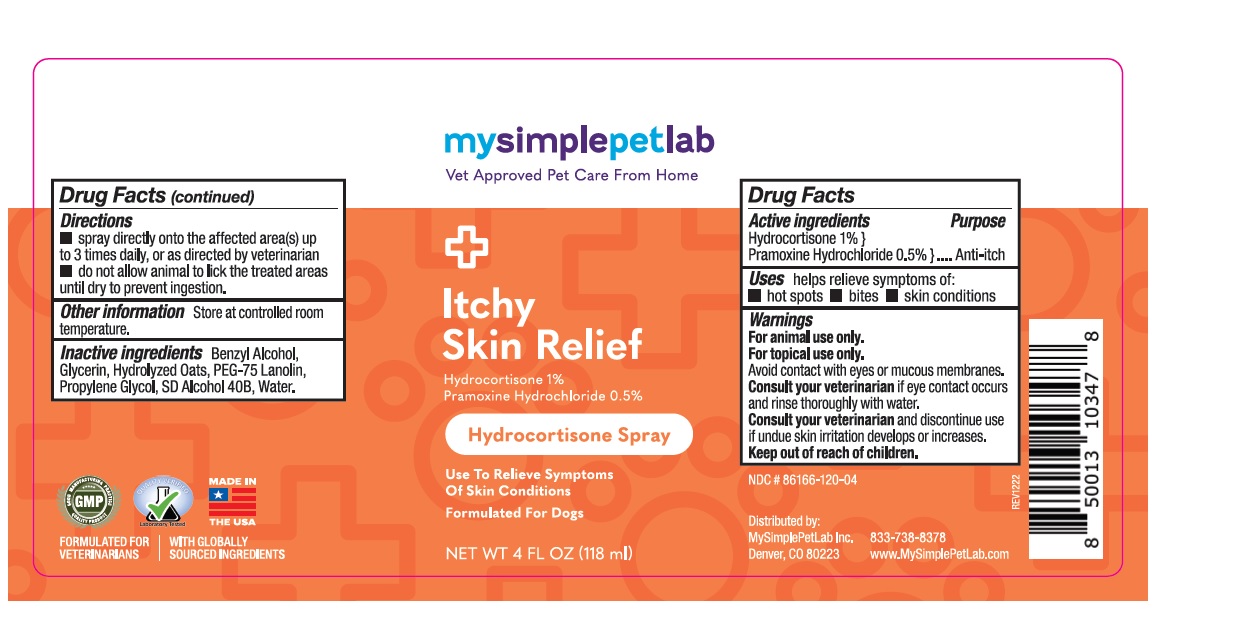 DRUG LABEL: MySimplePetLab Itchy Skin Relief
NDC: 86166-120 | Form: SPRAY
Manufacturer: Mysimplepetlab Inc
Category: animal | Type: OTC ANIMAL DRUG LABEL
Date: 20230316

ACTIVE INGREDIENTS: HYDROCORTISONE 1 g/100 mL; PRAMOXINE HYDROCHLORIDE 0.5 g/100 mL
INACTIVE INGREDIENTS: BENZYL ALCOHOL; GLYCERIN; OAT; PEG-75 LANOLIN; PROPYLENE GLYCOL; ALCOHOL; WATER

mysimplepetlab Itchy Skin Relief

Active ingredients

Hydrocortisone 1%

Pramoxine Hydrochloride 0.5%

Purpose

Anti-itch

Uses

helps relieve symptoms of:

• hot spots • bites • skin conditions

Warnings

For animal use only.
For topical use only.
Avoid contact with eyes or mucous membranes.
Consult your veterinarian if eye contact occurs and rinse thoroughly with water.
Consult your veterinarian and discontinue use if undue skin irritation develops or increases.
Keep out of reach of children.

Directions

- spray directly onto the affected area(s) up to 3 times daily, or as directed by veterinarian
- do not allow animal to lick the treated areas until dry to prevent ingestion.

Other information

Store at controlled room temperature.

Inactive ingredients

Benzyl Alcohol, Glycerin, Hydrolyzed Oats, PEG-75 Lanolin, Propylene Glycol, SD Alcohol 40B, Water.

Vet Approved Pet Care From Home

Formulated for Dogs

FORMULATED FOR VETERINARIANS

WITH GLOBALLY SOURCED INGREDIENTS

MADE IN THE USA

Distributed by:
MySimplePetLab Inc.
Denver, CO 80223

833-738-8378
www.MySimplePetLab.com